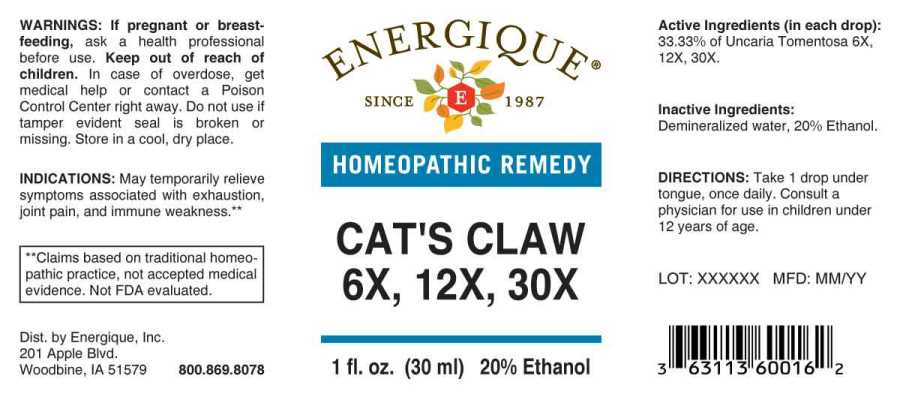 DRUG LABEL: Cats Claw
NDC: 44911-0432 | Form: LIQUID
Manufacturer: Energique, Inc.
Category: homeopathic | Type: HUMAN OTC DRUG LABEL
Date: 20241024

ACTIVE INGREDIENTS: CAT'S CLAW 6 [hp_X]/1 mL
INACTIVE INGREDIENTS: WATER; ALCOHOL

DRUG FACTS:

ACTIVE INGREDIENT:

(in each drop): 33.33% of Uncaria Tomentosa 6X, 12X, 30X.

INDICATIONS:

May temporarily relieve symptoms associated with exhaustion, joint pain, and immune weakness.**

**Claims based on traditional homeopathic practice, not accepted medical evidence. Not FDA evaluated.

WARNINGS:

If pregnant or breastfeeding, ask a health professional before use.

Keep out of reach of children. In case of overdose, get medical help or contact a Poison Control Center right away.

Do not use if tamper evident seal is broken or missing.

Store in a cool, dry place.

Keep out of reach of children. In case of overdose, get medical help or contact a Poison Control Center right away.

DIRECTIONS:

Take 1 drop under tongue, once daily. Consult a physician for use in children under 12 years of age.

INDICATIONS:

May temporarily relieve symptoms associated with exhaustion, joint pain, and immune weakness.**

**Claims based on traditional homeopathic practice, not accepted medical evidence. Not FDA evaluated.

INACTIVE INGREDIENTS:

Demineralized water, 20% Ethanol.

QUESTIONS:

Dist. by Energique, Inc.,

201 Apple Blvd.

Woodbine, IA 51579 800.869.8078

PACKAGE LABEL DISPLAY:

ENERGIQUE
SINCE 1987
HOMEOPATHIC REMEDY
CATS'S CLAW
6X, 12X, 30X
1 fl. oz. (30 ml)